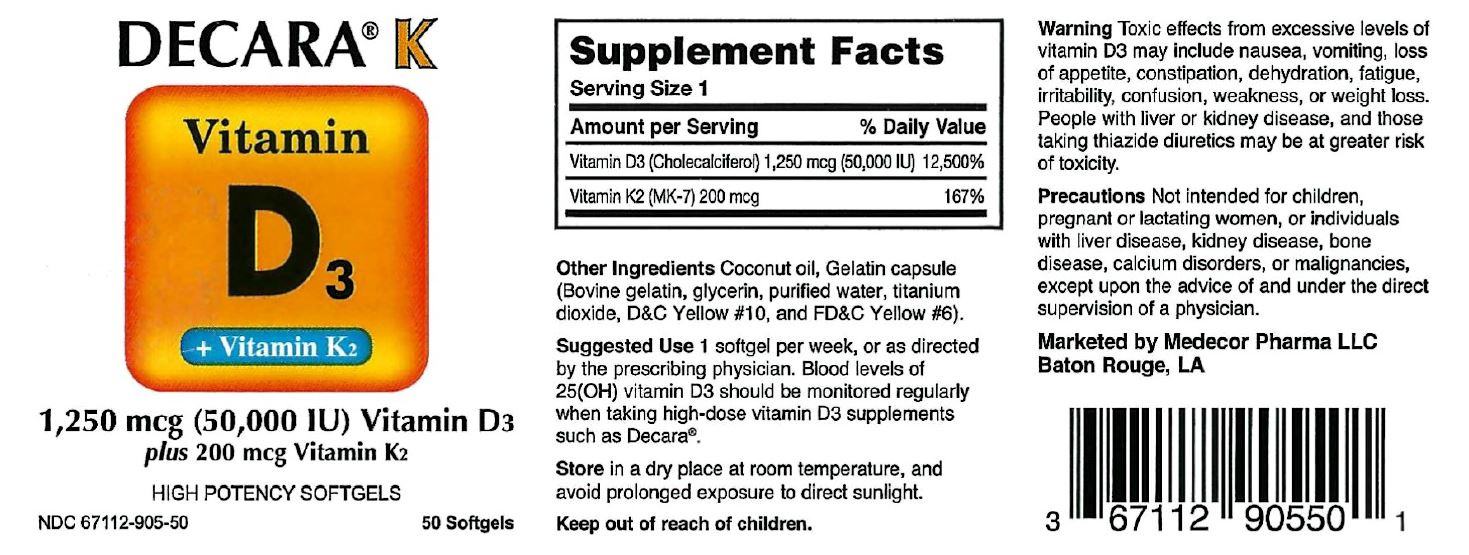 DRUG LABEL: DECARA K
NDC: 67112-905 | Form: CAPSULE
Manufacturer: Medecor Pharma, LLC
Category: other | Type: Dietary Supplement
Date: 20221227

ACTIVE INGREDIENTS: CHOLECALCIFEROL 1250 ug/1 1; PHYTONADIONE 200 ug/1 1
INACTIVE INGREDIENTS: COCONUT OIL; GELATIN TYPE B BOVINE (150 BLOOM); GLYCERIN; WATER; TITANIUM DIOXIDE; D&C YELLOW NO. 10; FD&C YELLOW NO. 6

MEDECOR PHARMA - DECARA K (67112-905)

STATEMENT OF IDENTITY

AMOUNT PER SERVING PERCENT DAILY VALUE

VITAMIN D3 (CHOLECALCIFEROL) 1,250 MCG (50,000 IU) 12.5OO%

VITAMIN K2 (MK-7) 200 MCG 167%